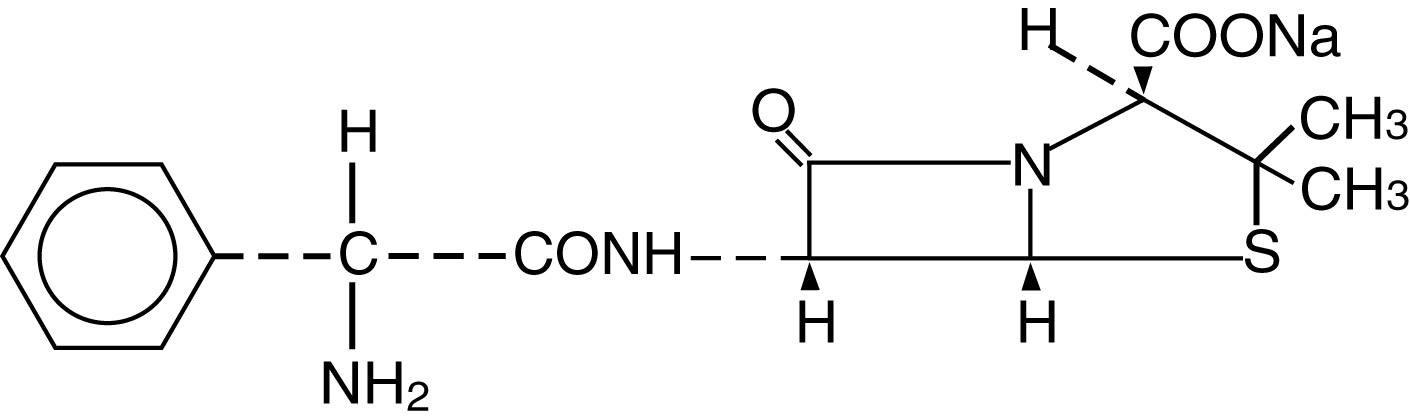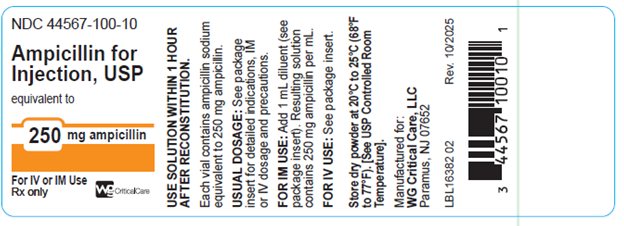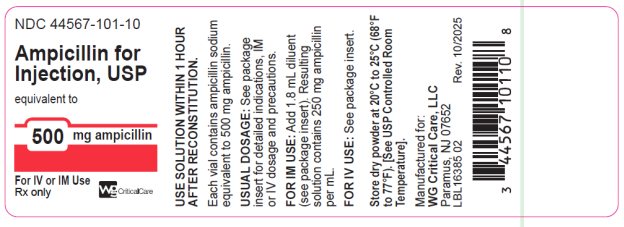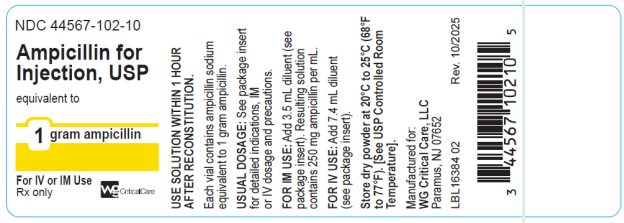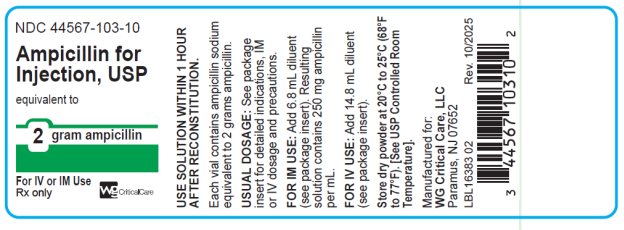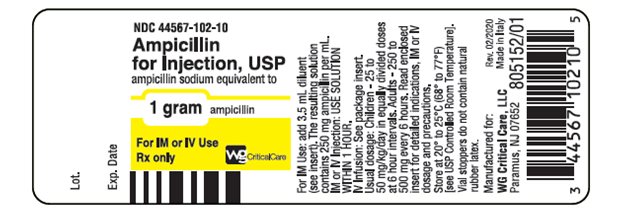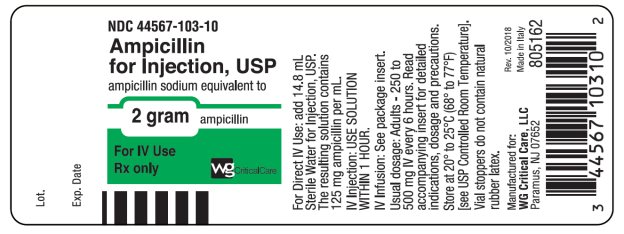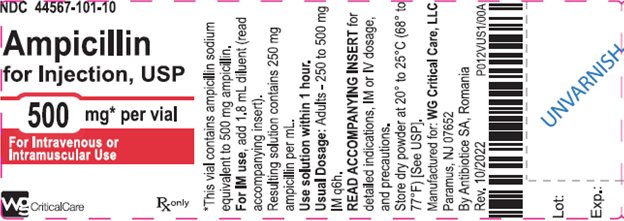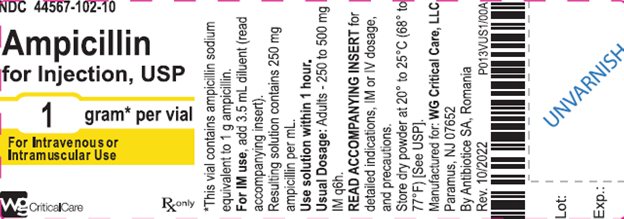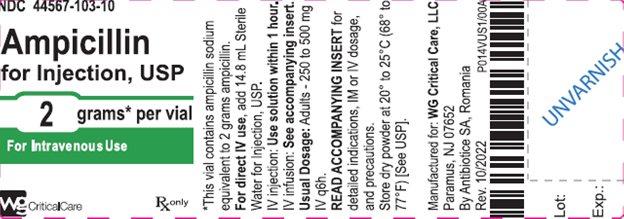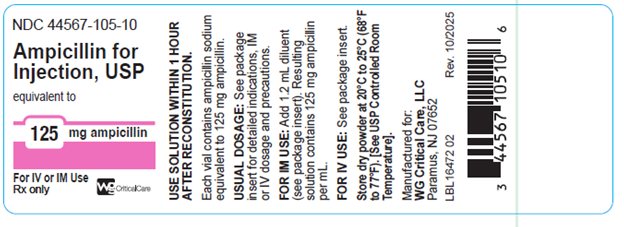 DRUG LABEL: Ampicillin
NDC: 44567-105 | Form: INJECTION, POWDER, FOR SOLUTION
Manufacturer: WG Critical Care, LLC
Category: prescription | Type: HUMAN PRESCRIPTION DRUG LABEL
Date: 20260205

ACTIVE INGREDIENTS: AMPICILLIN SODIUM 125 mg/1 1

Ampicillin for Injection, USP

Rx only

FOR INTRAMUSCULAR OR INTRAVENOUS USE

To reduce the development of drug-resistant bacteria and maintain the effectiveness of Ampicillin and other antibacterial drugs, Ampicillin for Injection, USP should be used only to treat infections that are proven or strongly suspected to be caused by bacteria.

DESCRIPTION

Ampicillin for Injection, USP the monosodium salt of [2S-[2a, 5a, 6b(S*)]]-6- [(aminophenylacetyl)amino]-3,3-dimethyl-7-oxo-4-thia-1-azabicyclo [3.2.0]heptane-2-carboxylic acid, is a synthetic penicillin. It is an antibacterial agent with a broad spectrum of bactericidal activity against both penicillin-susceptible Gram-positive organisms and many common Gram-negative pathogens. Ampicillin for Injection, USP is a dry, white to off-white powder. The reconstituted solution is clear, colorless and free from visible particulates. It has the following chemical structure:

The molecular formula is C16H18N3NaO4S, and the molecular weight is 371.39. The pH range of the reconstituted solution is 8.0 to 10.0. Ampicillin for Injection, USP contains 65.8 mg [2.9 mEq] sodium per gram ampicillin.

Ampicillin for Injection, USP is supplied in vials equivalent to 125 mg, 250 mg, 500 mg, 1 gram or 2 grams of ampicillin. It is to be administered by intravenous or intramuscular routes.

CLINICAL PHARMACOLOGY

Ampicillin for Injection, USP diffuses readily into most body tissues and fluids. However, penetration into the cerebrospinal fluid and brain occurs only when the meninges are inflamed. Ampicillin is excreted largely unchanged in the urine and its excretion can be delayed by concurrent administration of probenecid. Due to maturational changes in renal function, ampicillin half-life decreases as postmenstrual age (a sum of gestational age and postnatal age) increases for infants with postnatal age of less than 28 days. The active form appears in the bile in higher concentrations than those found in serum. Ampicillin is the least serum-bound of all the penicillins, averaging about 20% compared to approximately 60 to 90% for other penicillins. Ampicillin for Injection, USP is well tolerated by most patients and has been given in doses of 2 grams daily for many weeks without adverse reactions.

Microbiology:

While in vitro studies have demonstrated the susceptibility of most strains of the following organisms, clinical efficacy for infections other than those included in the INDICATIONS AND USAGE section has not been demonstrated.

Antibacterial Activity:

The following bacteria have been shown in in vitro studies to be susceptible to Ampicillin for Injection, USP:

Gram-positive Bacteria

Hemolytic and nonhemolytic streptococci

Streptococcus pneumoniae

Nonpenicillinase-producing staphylococci

Clostridium spp.

B. anthracis

Listeria monocytogenes

Most strains of enterococci.

Gram-negative Bacteria

H. influenzae

N. gonorrhoeae

N. meningitidis

Proteus mirabilis

Many strains of Salmonella, Shigella, and E. coli.

AMPICILLIN does not resist destruction by penicillinase.

Susceptibility Testing

For specific information regarding susceptibility test interpretive criteria and associated test methods and quality control standards recognized by FDA for this drug, please see: https://www.fda.gov/STIC.

INDICATIONS AND USAGE

Ampicillin for Injection, USP is indicated in the treatment of infections caused by susceptible strains of the designated organisms in the following conditions:

Respiratory Tract Infections caused by S. pneumoniae, Staphylococcus aureus (penicillinase and non-penicillinase producing), H. influenzae and Group A beta-hemolytic Streptococci.

Bacterial Meningitis caused by E. coli, Group B Streptococci, and other Gram-negative bacteria (Listeria monocytogenes, N. meningitidis). The addition of an aminoglycoside with ampicillin may increase its effectiveness against Gram-negative bacteria.

Septicemia and Endocarditis caused by susceptible Gram-positive organisms including Streptococcus spp., penicillin-G-susceptible staphylococci and enterococci. Gram-negative sepsis caused by E. coli, Proteus mirabilis and Salmonella spp. responds to ampicillin. Endocarditis due to enterococcal strains usually respond to intravenous therapy. The addition of an aminoglycoside may enhance the effectiveness of ampicillin when treating streptococcal endocarditis.

Urinary Tract Infections caused by sensitive strains of E. coli and Proteus mirabilis.

Gastrointestinal Infections caused by Salmonella typhi (typhoid fever), other Salmonella spp. and Shigella spp. (dysentery) usually respond to oral or intravenous therapy.

Bacteriology studies to determine the causative organisms and their susceptibility to ampicillin should be performed. Therapy may be instituted prior to obtaining results of susceptibility testing.

It is advisable to reserve the parenteral form of this drug for moderately severe and severe infections and for patients who are unable to take the oral forms. A change to oral ampicillin may be made as soon as appropriate. Indicated surgical procedures should be performed.

To reduce the development of drug-resistant bacteria and maintain the effectiveness of Ampicillin for Injection, USP and other antibacterial drugs, Ampicillin for Injection, USP should be used only to treat or prevent infections that are proven or strongly suspected to be caused by susceptible bacteria. When culture and susceptibility information are available, they should be considered in selecting or modifying antibacterial therapy. In the absence of such data, local epidemiology and susceptibility patterns may contribute to the empiric selection of therapy.

CONTRAINDICATIONS

A history of a previous hypersensitivity reaction to any of the penicillins is a contraindication.

WARNINGS

Serious and occasionally fatal hypersensitivity (anaphylactoid) reactions have been reported in patients on penicillin therapy. Although anaphylaxis is more frequent following parenteral therapy, it has occurred in patients on oral penicillins. These reactions are more apt to occur in individuals with a history of penicillin hypersensitivity and/or a history of sensitivity to multiple allergens.

There have been well-documented reports of individuals with a history of penicillin hypersensitivity reactions who have experienced severe hypersensitivity reactions when treated with a cephalosporin. Before initiating therapy with a penicillin, careful inquiry should be made concerning previous hypersensitivity reactions to penicillins, cephalosporins, and other allergens. If an allergic reaction occurs, the drug should be discontinued and appropriate therapy instituted.

SERIOUS ANAPHYLACTOID REACTIONS REQUIRE IMMEDIATE EMERGENCY TREATMENT WITH EPINEPHRINE, OXYGEN, INTRAVENOUS STEROIDS, AND AIRWAY MANAGEMENT, INCLUDING INTUBATION, SHOULD ALSO BE ADMINISTERED AS INDICATED.

Clostridium difficile associated diarrhea (CDAD) has been reported with use of nearly all antibacterial agents, including Ampicillin for Injection, USP, and may range in severity from mild diarrhea to fatal colitis. Treatment with antibacterial agents alters the normal flora of the colon leading to overgrowth of C. difficile.

C. difficile produces toxins A and B which contribute to the development of CDAD. Hypertoxin producing strains of C. difficile cause increased morbidity and mortality, as these infections can be refractory to antimicrobial therapy and may require colectomy. CDAD must be considered in all patients who present with diarrhea following antibacterial drug use. Careful medical history is necessary since CDAD has been reported to occur over two months after the administration of antibacterial agents.

If CDAD is suspected or confirmed, ongoing antibacterial drug use not directed against C. difficile may need to be discontinued. Appropriate fluid and electrolyte management, protein supplementation, antibacterial treatment of C. difficile, and surgical evaluation should be instituted as clinically indicated.

PRECAUTIONS

General

Prescribing Ampicillin for Injection, USP in the absence of a proven or strongly suspected bacterial infection or a prophylactic indication is unlikely to provide benefit to the patient and increases the risk of the development of drug-resistant bacteria.

The possibility of superinfections with mycotic organisms or bacterial pathogens should be kept in mind during therapy. In such cases, discontinue the drug and substitute appropriate treatment.

A high percentage (43 to 100 percent) of patients with infectious mononucleosis who receive ampicillin develop a skin rash. Typically, the rash appears 7 to 10 days after the start of oral ampicillin therapy and remains for a few days to a week after the drug is discontinued. In most cases, the rash is maculopapular; pruritic and generalized. Therefore, the administration of ampicillin is not recommended in patients with mononucleosis. It is not known whether these patients are truly allergic to ampicillin.

Information for Patients

Patients should be counseled that antibacterial drugs including Ampicillin for Injection, USP should only be used to treat bacterial infections. They do not treat viral infections (e.g., the common cold). When Ampicillin for Injection, USP is prescribed to treat a bacterial infection, patients should be told that although it is common to feel better early in the course of therapy, the medication should be taken exactly as directed.

Skipping doses or not completing the full course of therapy may (1) decrease the effectiveness of the immediate treatment and (2) increase the likelihood that bacteria will develop resistance and will not be treatable by Ampicillin for Injection, USP or other antibacterial drugs in the future.

Diarrhea is a common problem caused by antibacterials which usually ends when the antibacterial is discontinued. Sometimes after starting treatment with antibacterials, patients can develop watery and bloody stools (with or without stomach cramps and fever) even as late as two or more months after having taken the last dose of the antibacterial. If this occurs, patients should contact their physician as soon as possible.

Laboratory Tests

As with any potent drug, periodic assessment of organ system function, including renal, hepatic and hematopoietic, should be made during prolonged therapy.

Transient elevation of serum transaminase has been observed following administration of ampicillin. The significance of this finding is not known.

Drug Interactions

The concurrent administration of allopurinol and ampicillin increases substantially the incidence of skin rashes in patients receiving both drugs as compared to patients receiving ampicillin alone. It is not known whether this potentiation of ampicillin rashes is due to allopurinol or the hyperuricemia present in these patients.

Drug/Laboratory Test Interactions

With high urine concentrations of ampicillin, false-positive glucose reactions may occur if Clinitest, Benedict’s Solution, or Fehling’s Solution are used. Therefore, it is recommended that glucose tests based on enzymatic glucose oxidase reactions (such as Clinistix or Tes-Tape) be used.

Carcinogenesis, Mutagenesis, and Impairment of Fertility

No long-term animal studies have been conducted with this drug.

Pregnancy Category B:

Reproduction studies have been performed in laboratory animals at doses several times the human dose and have revealed no evidence of adverse effects due to ampicillin. There are, however, no adequate and well-controlled studies in pregnant women. Because animal reproduction studies are not always predictive of human response, this drug should be used during pregnancy only if clearly needed.

Labor and Delivery

Oral ampicillin-class antibacterials are poorly absorbed during labor. Studies in guinea pigs showed that intravenous administration of ampicillin slightly decreased the uterine tone and frequency of contractions, but moderately increased the height and duration of contractions. However, it is not known whether use of these drugs in humans during labor or delivery has immediate or delayed adverse effects on the fetus, prolongs the duration of labor, or increases the likelihood that forceps delivery or other obstetrical intervention or resuscitation of the newborn will be necessary.

Nursing Mothers

Ampicillin is excreted in trace amounts in human milk. Therefore, caution should be exercised when ampicillin-class antibacterials are administered to a nursing woman.

Pediatric Use

Guidelines for the administration of these drugs to children, including neonates are presented in DOSAGE AND ADMINISTRATION.

ADVERSE REACTIONS

As with other penicillins, it may be expected that untoward reactions will be essentially limited to sensitivity phenomena. They are more likely to occur in individuals who have previously demonstrated hypersensitivity to penicillins and in those with a history of allergy, asthma, hay fever or urticaria. The following adverse reactions have been reported as associated with the use of ampicillin:

Gastrointestinal

Glossitis, stomatitis, black “hairy” tongue, nausea, vomiting, enterocolitis, pseudomembranous colitis, and diarrhea. (These reactions are usually associated with oral dosage forms.)

Hypersensitivity Reactions

Skin rashes and urticaria have been reported frequently. A few cases of exfoliative dermatitis and erythema multiforme have been reported. Linear IgA bullous dermatosis has been reported. Anaphylaxis is the most serious reaction experienced and has usually been associated with the parenteral dosage form.

Note: Urticaria, other skin rashes, and serum sickness-like reactions may be controlled with antihistamines and, if necessary, systemic corticosteroids.

Whenever such reactions occur, ampicillin should be discontinued, unless, in the opinion of the physician, the condition being treated is life-threatening and amenable only to ampicillin therapy. Serious anaphylactic reactions require the immediate use of epinephrine, oxygen, and intravenous steroids.

Liver

A moderate rise in serum glutamic oxaloacetic transaminase (SGOT) has been noted, particularly in infants, but the significance of this finding is unknown. Mild transitory SGOT elevations have been observed in individuals receiving larger (two to four times) than usual and oft-repeated intramuscular injections. Evidence indicates that glutamic oxaloacetic transaminase (GOT) is released at the site of intramuscular injection of Ampicillin for Injection and that the presence of increased amounts of this enzyme in the blood does not necessarily indicate liver involvement.

Hemic and Lymphatic Systems

Anemia, thrombocytopenia, thrombocytopenic purpura, eosinophilia, leukopenia, and agranulocytosis have been reported during therapy with the penicillins. These reactions are usually reversible on discontinuation of therapy and are believed to be hypersensitivity phenomena.

Central Nervous System

Seizures.

OVERDOSAGE

In cases of overdose, discontinue medication, treat symptomatically and institute supportive measures as required. In patients with renal function impairment, ampicillin-class antibacterials can be removed by hemodialysis but not peritoneal dialysis.

DOSAGE AND ADMINISTRATION

Infections of the respiratory tract and soft tissues.

Patients weighing 40 kg (88 lbs) or more: 250 mg to 500 mg every 6 hours.

Patients weighing less than 40 kg (88 lbs): 25 to 50 mg/kg/day in equally divided doses at 6- to 8-hour intervals.

Infections of the gastrointestinal and genitourinary tracts (including those caused by Neisseria gonorrhoeae in females).

Patients weighing 40 kg (88 lbs) or more: 500 mg every 6 hours.

Patients weighing less than 40 kg (88 lbs): 50 mg/kg/day in equally divided doses at 6- to 8-hour intervals.

In the treatment of chronic urinary tract and intestinal infections, frequent bacteriological and clinical appraisal is necessary. Smaller doses than those recommended above should not be used. Higher doses should be used for stubborn or severe infections. In stubborn infections, therapy may be required for several weeks. It may be necessary to continue clinical and/or bacteriological follow-up for several months after cessation of therapy.

Urethritis in males due to N. gonorrhoeae:

Adults: Two doses of 500 mg each at an interval of 8 to 12 hours.

Treatment may be repeated if necessary or extended if required.

In the treatment of complications of gonorrheal urethritis, such as prostatitis and epididymitis, prolonged and intensive therapy is recommended. Cases of gonorrhea with a suspected primary lesion of syphilis should have darkfield examinations before receiving treatment. In all other cases where concomitant syphilis is suspected, monthly serological tests should be made for a minimum of four months.

The doses for the preceding infections may be given by either the intramuscular or intravenous route. A change to oral ampicillin may be made when appropriate.

Bacterial Meningitis.

Adults and children: 150 to 200 mg/kg/day in equally divided doses every 3 to 4 hours. (Treatment may be initiated with intravenous drip therapy and continued with intramuscular injections.) The doses for other infections may be given by either the intravenous or intramuscular route.

Neonates (less than or equal to 28 days of postnatal age): Dosage should be based on Gestational age and Postnatal age according to Table 1.

Table 1: Dosage in Neonates (less than or equal to 28 days of postnatal age) for Bacterial Meningitis and Septicemia

Gestational age (weeks) | Postnatal age (days) | Dosage
less than or equal to 34 | less than or equal to 7 | 100 mg/kg/day in equally divided doses every 12 hours
less than or equal to 34 | greater than or equal to 8 and less than 28 | 150 mg/kg/day in equally divided doses every 12 hours
greater than 34 | less than or equal to 28 | 150 mg/kg/day in equally divided doses every 8 hours

Septicemia.

Adults and children: 150 to 200 mg/kg/day. Start with intravenous administration for at least three days and continue with the intramuscular route every 3 to 4 hours.

Neonates (less than or equal to 28 days of postnatal age): Dosage should be based on Gestational age and Postnatal age according to Table 1 (above).

Treatment of all infections should be continued for a minimum of 48 to 72 hours beyond the time that the patient becomes asymptomatic or evidence of bacterial eradication has been obtained. A minimum of 10 days treatment is recommended for any infection caused by Group A beta-hemolytic streptococci to help prevent the occurrence of acute rheumatic fever or acute glomerulonephritis.

DIRECTIONS FOR USE

Use only freshly prepared solutions. Intramuscular and intravenous injections should be administered within one hour after preparation, since the potency may decrease significantly after this period.

Parenteral drug products should be inspected visually for particulate matter and discoloration prior to administration, whenever solution and container permit.

For Intramuscular Use: Dissolve contents of a vial with the amount of Sterile Water for Injection, USP or Bacteriostatic Water for Injection, USP, listed in the table below:

NDC | Label Claim | Recommended Amount of Diluent | Withdrawable Volume | Concentration (in mg/mL)
44567-105-10 | 125 mg | 1.2 mL | 1 mL | 125 mg
44567-100-10 | 250 mg | 1 mL | 1 mL | 250 mg
44567-101-10 | 500 mg | 1.8 mL | 2 mL | 250 mg
44567-102-10 | 1 gram | 3.5 mL | 4 mL | 250 mg
44567-103-10 | 2 grams | 6.8 mL | 8 mL | 250 mg

While Ampicillin for Injection, USP 1 g and 2 g, are primarily for intravenous use, they may be administered intramuscularly when the 250 mg or 500 mg vials are unavailable. In such instances, dissolve in 3.5 or 6.8 mL Sterile Water for Injection, USP or Bacteriostatic Water for Injection, USP, respectively. The resulting solution will provide a concentration of 250 mg per mL.

Ampicillin for Injection, USP 125 mg, is intended primarily for pediatric use. It also serves as a convenient dosage form when small parenteral doses of the antibiotic are required.

Note: Bacteriostatic Water for Injection, USP is not to be used as a diluent when the product will be used in newborns.

For Direct Intravenous Use

Add 5 mL Sterile Water for Injection, USP, or Bacteriostatic Water for Injection, USP to the 125 mg, 250 mg, and 500 mg vials and administer slowly over a 3 to 5 minute period. Ampicillin for Injection, USP 1 g or 2 g, may also be given by direct intravenous administration. Dissolve in 7.4 or 14.8 mL Sterile Water for Injection, USP, or Bacteriostatic Water for Injection, USP, respectively, and administer slowly over at least 10 to 15 minutes. CAUTION: More rapid administration may result in convulsive seizures.

For Administration by Intravenous Drip:

Reconstitute as directed above (For Direct Intravenous Use) prior to diluting with Intravenous Solution. Stability studies on ampicillin sodium at several concentrations in various intravenous solutions indicate the drug will lose less than 10% activity at the temperatures noted for the time periods stated.

Room Temperature (25°C)
Diluent | Concentrations | Stability Periods
Sterile Water for Injection | up to 30 mg/mL | 8 hours
0.9% Sodium Chloride Injection, USP | up to 30 mg/mL | 8 hours
5% Dextrose Injection, USP | 10 to 20 mg/mL | 1 hour
5% Dextrose Injection, USP | up to 2 mg/mL | 2 hours
5% Dextrose and 0.45% Sodium Chloride Injection, USP | up to 2 mg/mL | 2 hours
Lactated Ringer’s Injection, USP | up to 30 mg/mL | 8 hours
Refrigerated (4°C)
Sterile Water for Injection | 30 mg/mL | 48 hours
Sterile Water for Injection | up to 20 mg/mL | 72 hours
0.9% Sodium Chloride Injection, USP | 30 mg/mL | 24 hours
0.9% Sodium Chloride Injection, USP | up to 20 mg/mL | 48 hours
Lactated Ringer’s Injection, USP | up to 30 mg/mL | 24 hours
5% Dextrose Injection, USP | up to 20 mg/mL | 1 hour
5% Dextrose and 0.45% Sodium Chloride Injection, USP | up to 10 mg/mL | 1 hour

Only those solutions listed above should be used for the intravenous infusion of Ampicillin for Injection, USP. The concentrations should fall within the range specified. The drug concentration and the rate and volume of the infusion should be adjusted so that the total dose of ampicillin is administered before the drug loses its stability in the solution in use.

Piggyback IV Package: These glass vials contain the labeled quantity of Ampicillin for Injection and are intended for intravenous administration. The diluent and volume are specified on the label of each package.

HOW SUPPLIED

Ampicillin for Injection, USP equivalent to 125 mg, 250 mg, 500 mg, 1 or 2 grams ampicillin as the sodium salt per vial is supplied as follows:

NDC 44567-105-10; NDC 44567-100-10 | 125 mg vial; 250 mg vial | (Package of 10); (Package of 10)
NDC 44567-101-10 | 500 mg vial | (Package of 10)
NDC 44567-102-10 | 1 gram vial | (Package of 10)
NDC 44567-103-10 | 2 gram vial | (Package of 10)

Ampicillin for Injection, USP dry powder should be stored at 20° to 25°C (68° to 77°F) [See USP Controlled Room Temperature].

To report SUSPECTED ADVERSE REACTIONS, contact WG Critical Care, LLC at 1-866-562-4708 or the FDA at 1-800-FDA-1088 or www.fda.gov/medwatch for voluntary reporting of adverse reactions.

Clinitest is a registered trademark of Miles, Inc.

Clinistix is a registered trademark of Bayer Corporation.

Tes-Tape is a registered trademark of Eli Lilly Company.

Manufactured for:

WG Critical Care, LLC

Paramus, NJ 07652

Revised: November 2024

Package/Label Display Panel

44567-105-10

Ampicillin for Injection, USP 125 mg

FOR IM OR IV USE

Rx Only

PRINCIPAL DISPLAY PANEL

NDC 44567-100-10

Ampicillin for Injection, USP 250 mg

FOR IM OR IV USE

Rx Only

PRINCIPAL DISPLAY PANEL

NDC 44567-101-10

Ampicillin for Injection, USP 500 mg

FOR IM OR IV USE

Rx Only

PRINCIPAL DISPLAY PANEL

NDC 44567-102-10

Ampicillin for Injection, USP 1 gram

FOR IM OR IV USE

Rx Only

PRINCIPAL DISPLAY PANEL

NDC 44567-103-10

Ampicillin for Injection, USP 2 gram

FOR IM OR IV USE

Rx Only

Package/Label Display Panel

NDC 44567-102-10

Ampicillin for Injection, USP 1 gram

FOR IM OR IV USE

Rx Only

Package/Label Display Panel

NDC 44567-103-10

Ampicillin for Injection, USP 2 gram

FOR IM OR IV USE

Rx Only

Package/Label Display Panel

NDC 44567-101-10

Ampicillin for Injection, USP 500 mg

FOR IM OR IV USE

Rx Only

Package/Label Display Panel

NDC 44567-103-10

Ampicillin for Injection, USP 2 gram

FOR IV USE

Rx Only